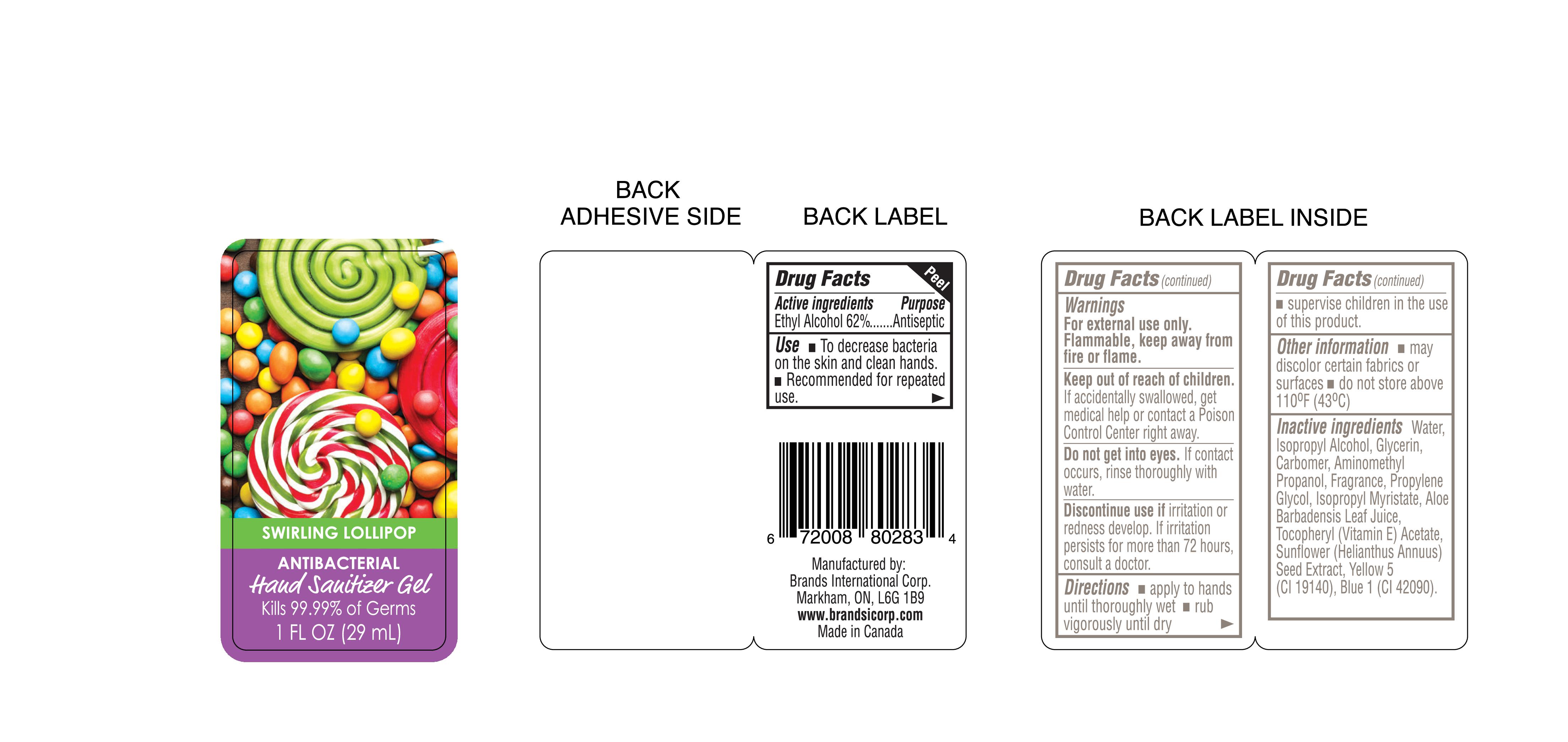 DRUG LABEL: SWIRLING LOLLIPOP
NDC: 50157-114 | Form: GEL
Manufacturer: Brands International Corp
Category: otc | Type: HUMAN OTC DRUG LABEL
Date: 20151102

ACTIVE INGREDIENTS: ALCOHOL 620 mL/1000 mL
INACTIVE INGREDIENTS: CARBOMER 940; PROPYLENE GLYCOL; ISOPROPYL MYRISTATE; ALOE VERA LEAF; ALPHA-TOCOPHEROL ACETATE; SUNFLOWER SEED; FD&C YELLOW NO. 5; FD&C BLUE NO. 1; WATER; ISOPROPYL ALCOHOL; GLYCERIN; AMINOMETHYLPROPANOL

PACKAGE LABEL

SWIRLING LOLLIPOP

ANTIBACTERIAL

Hand Sanitizer Gel

Kills 99.99% of Germs

1 FL OZ (29ml)

ACTIVE INGREDIENTS: Ethyl Alcohol 62%

PURPOSE

Antiseptic

Use

- To decrease bacteria on the skin and clean hands.
- Recommended for repeated use.

Warnings

For external use only.

Flammable, keep away from fire or flame.

Keep out of reach of children. If accidentally swallowed get medical help or contact a Poison Control Center right away.

WHEN USING

Do not get into eyes. If contact occurs, rinse thoroughly with water.

ASK DOCTOR

Discontinue use if irritation or redness develop. If irritation persists for more than 72 hours, consult a doctor.

Directions

- apply to hands until thoroughly wet
- rub vigorously until dry
- supervise children in the use of this product

OTHER SAFETY INFORMATION

- may discolor certain fabrics or surfaces
- do not store above 110ºF (43ºC)

INACTIVE INGREDIENT

Water, Isopropyl Alcohol, Glycerin, Carbomer, Aminomethyl Propanol, Fragrance, Propylene Glycol, Isopropyl Myristate, Aloe Barbadensis Leaf Juice, Tocopheryl (Vitamin E) Acetate, Sunflower (Helianthus Annuus) Seed Extract, Yellow 5 (Cl 19140), Blue 1 (Cl 42090)